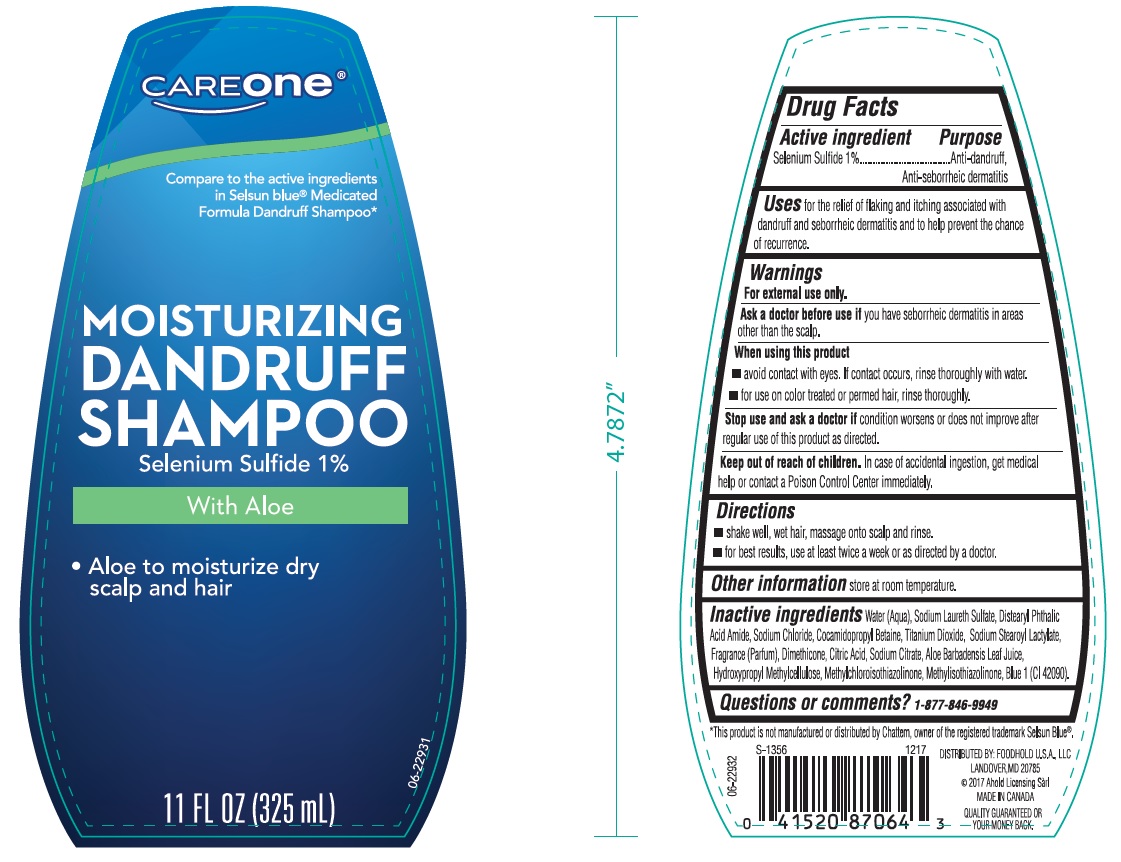 DRUG LABEL: CareOne Moisturizing Dandruff with Aloe
NDC: 41520-623 | Form: SHAMPOO
Manufacturer: American Sales Company
Category: otc | Type: HUMAN OTC DRUG LABEL
Date: 20180328

ACTIVE INGREDIENTS: SELENIUM SULFIDE 10 mg/1 mL
INACTIVE INGREDIENTS: WATER; SODIUM LAURETH SULFATE; DISTEARYL PHTHALAMIC ACID; SODIUM CHLORIDE; COCAMIDOPROPYL BETAINE; SODIUM STEAROYL LACTYLATE; DIMETHICONE; CITRIC ACID MONOHYDRATE; SODIUM CITRATE; ALOE VERA LEAF; HYPROMELLOSES; METHYLCHLOROISOTHIAZOLINONE; METHYLISOTHIAZOLINONE; TITANIUM DIOXIDE; FD&C BLUE NO. 1

Drug Facts

Active ingredient

Selenium Sulfide 1%

Purpose

Anti-dandruff, anti-seborrheic dermatitis

Uses

for the relief of flaking and itching associated with dandruff and seborrheic dermatitis and to help prevent the chance of recurrence.

Warnings

For external use only.

Ask a doctor before use if

you have seborrheic dermatitis in areas other than the scalp.

When using this product

- avoid contact with eyes. If contact occurs, rinse thoroughly with water.
- for use on color treated or permed hair, rinse thoroughly.

Stop use and ask a doctor if

condition worsens or does not improve after regular use of this product as directed.

Keep out of reach of children.

In case of accidental ingestion, get medical help or contact a Poison Control Center immediately.

Directions

- shake well, wet hair, massage onto scalp and rinse.
- for best results, use at least twice a week or as directed by a doctor.

Other information

store at room temperature.

Inactive ingredients

Water (Aqua), Sodium Laureth Sulfate, Distearyl Phthalic Acid Amide, Sodium Chloride, Cocamidopropyl Betaine, Titanium Dioxide, Sodium Stearoyl Lactylate, Fragrance (Parfum), Dimethicone, Citric Acid, Sodium Citrate, Aloe Barbadensis Leaf Juice, Hydroxypropyl Methylcellulose, Methylchloroisothiazolinone, Methylisothiazolinone, Blue 1 (CI 42090).

Questions or comments?

1-877-846-9949